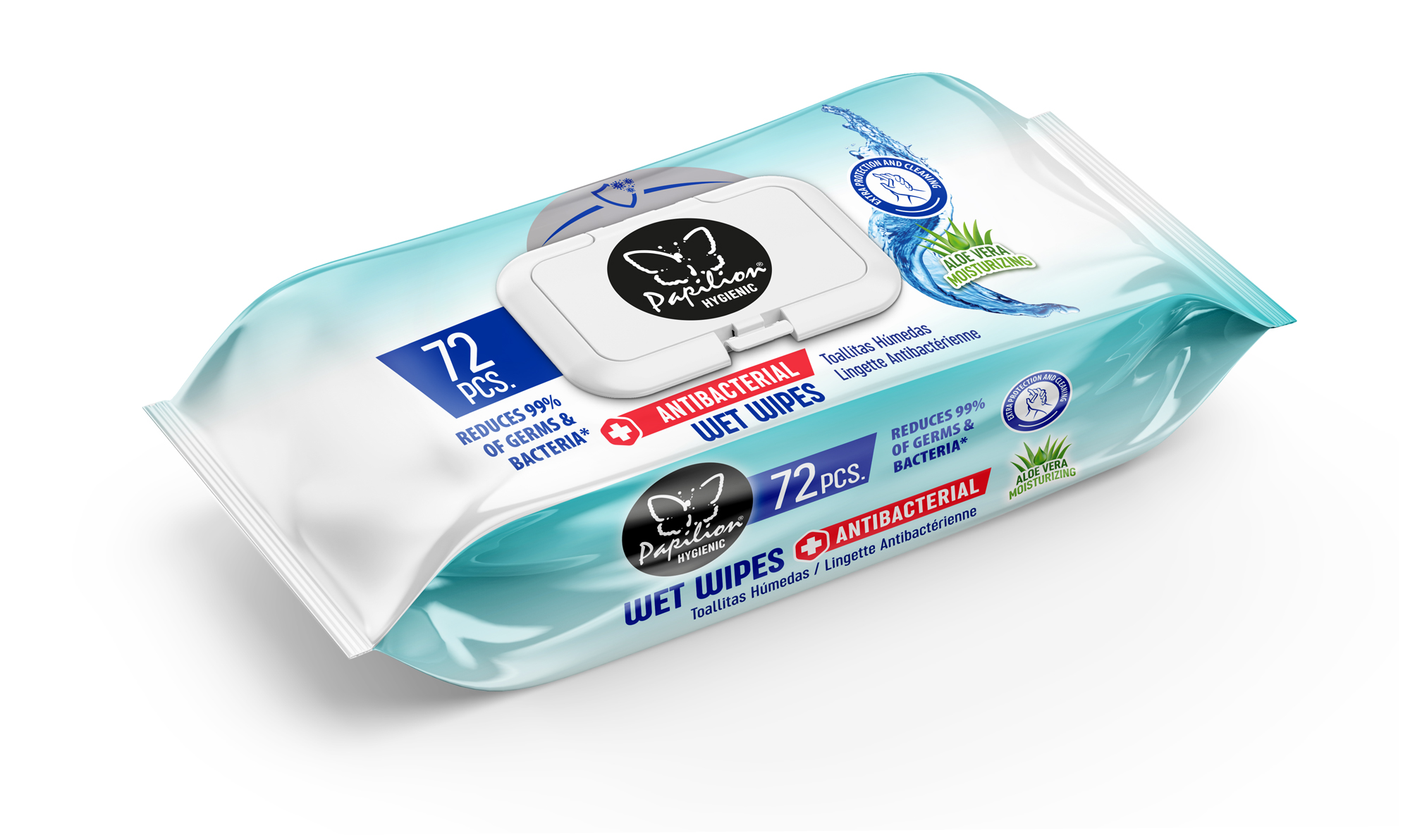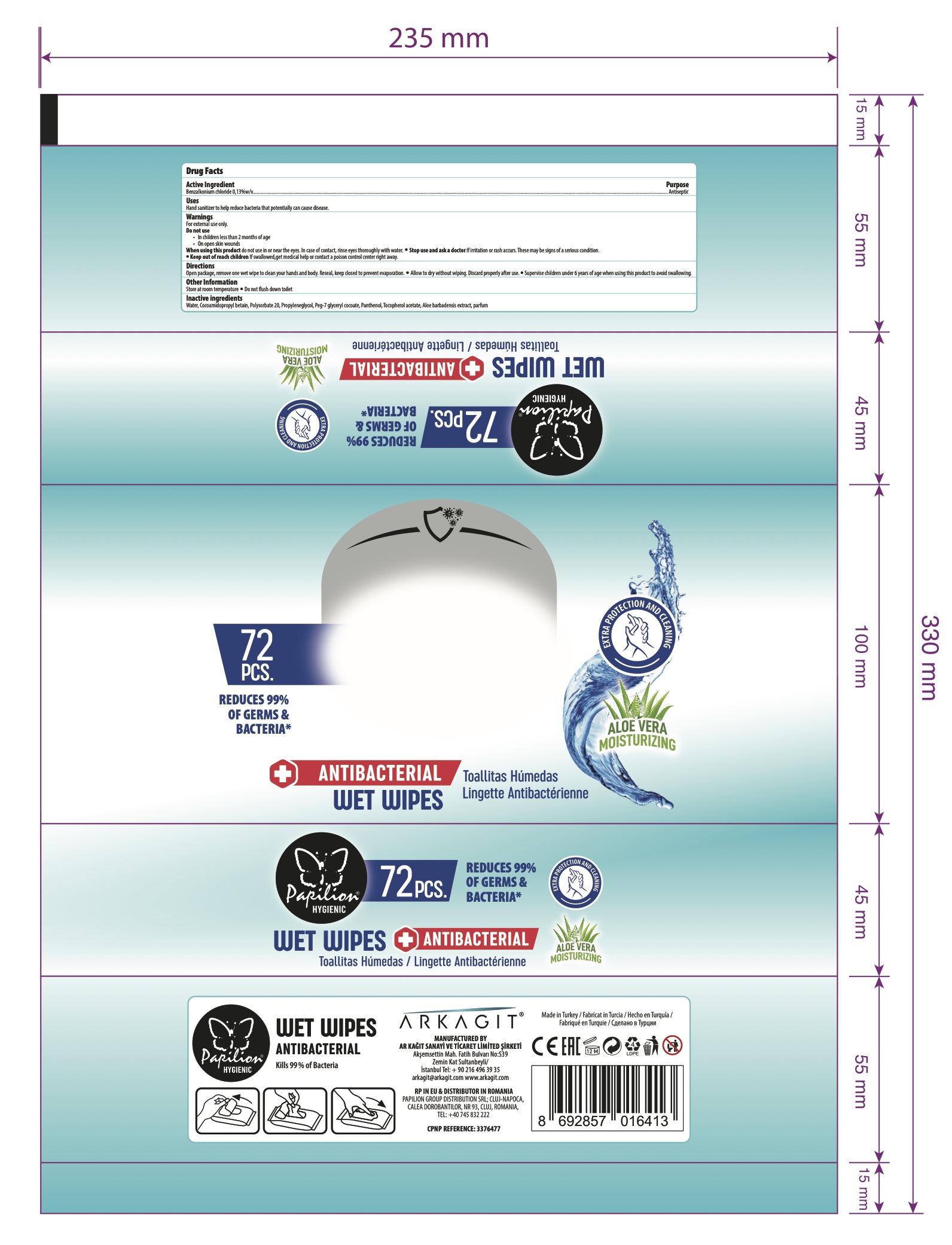 DRUG LABEL: PAPILION HYGIENIC ANTIBACTERIAL WET WIPES
NDC: 79262-170 | Form: CLOTH
Manufacturer: AR KAGIT SAN. ve TIC. LTD. STI.
Category: otc | Type: HUMAN OTC DRUG LABEL
Date: 20210228

ACTIVE INGREDIENTS: BENZALKONIUM CHLORIDE 0.13 mg/100 mL
INACTIVE INGREDIENTS: PROPYLENE GLYCOL 0.2 mg/100 mL; WATER 98.8 mg/100 mL; COCAMIDOPROPYL BETAINE 0.125 mg/100 mL; PEG-7 GLYCERYL COCOATE 0.15 mg/100 mL; .ALPHA.-TOCOPHEROL ACETATE 0.1 mg/100 mL; PANTHENOL 0.05 mg/100 mL; FRAGRANCE FLORAL ORC0902236 0.225 mg/100 mL; POLYSORBATE 20 0.225 mg/100 mL; ALOE ARBORESCENS LEAF 0.1 mg/100 mL

Papilion HYGIENIC WET WIPES ANTIBACTERIAL

Islak Mendil

EXTA PROTECTION AND CLEANING

KILLS 99.9% OF GERMS & BACTERIA

Active Ingredient(s)

Benzalkonium chloride 0.13 % w/v . Purpose: Antiseptic

Purpose

Antiseptic,

Papilion HYGIENIC WET WIPES ANTIBACTERIAL

Uses

Hand sanitizer to help reduce bacteria that potentially can cause disease.

Warnings

For external use only.

Do not use

in children less than 2 months of age

On open skin wounds

When using this product, do not use in or near the eyes. In case of contact, rinse eyes thoroughly with water.

Keep out of reach of children. If swallowed, get medical help or contact a Poison Control Center right away.

When using this product, do not use in or near the eyes. In case of contact, rinse eyes thoroughly with water.

Stop use and ask a doctor if irritation or rash develops and continues for more than 72 hours.

Keep out of reach of children. If swallowed, get medical help or contact a Poison Control Center right away.

Directions

Open package, remove one wet wipe to clean your hands and body. Reseal, keep closed to prevent evaporation.

Allow to dry without wiping. Discard propearly after use.

Supervise children under 6 years of age when using this product to avoid swallowing.

Other information

Store at room temperature

Do not flush down toilet.

Inactive ingredients

Water, Cocamidopropyl Betain, Polysorbate 20, Propylene Glycol, PEG-7 Glyceryl Cocoate, Panthenol, Tocopherol Acetate, Aloe barbadensis Extract, Parfum.

Package Label - Principal Display Panel

NDC: 79262-170-01